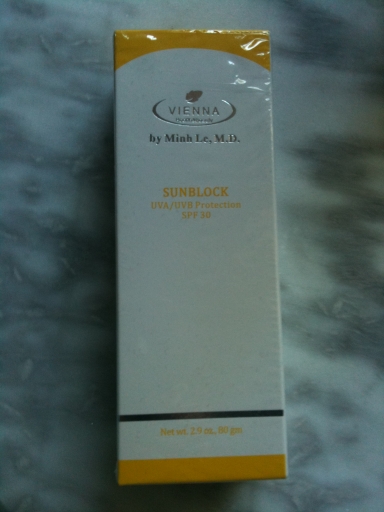 DRUG LABEL: Sunblock
NDC: 52625-101 | Form: LOTION
Manufacturer: Vienna Health and Beauty Corporation
Category: otc | Type: HUMAN OTC DRUG LABEL
Date: 20100701

ACTIVE INGREDIENTS: TITANIUM DIOXIDE 6 g/80 g; OCTINOXATE 5 g/80 g
INACTIVE INGREDIENTS: MEDIUM-CHAIN TRIGLYCERIDES; C12-15 ALKYL BENZOATE; GLYCERIN; CETYL ALCOHOL; STEARYL ALCOHOL; ISOPROPYL MYRISTATE; PROPYLENE GLYCOL; CETEARETH-25; GLYCERYL MONOSTEARATE; STEARIC ACID; ALPHA-TOCOPHEROL ACETATE; TROLAMINE; DIAZOLIDINYL UREA; METHYLPARABEN; PROPYLPARABEN; ALLANTOIN; BUTYLATED HYDROXYTOLUENE ; WATER

Drug Facts

Active Ingredients: Purpose
Titanium Dioxide 8% Sunscreen
Octyl Methoxycinnamate 6% Sunscreen
Other Ingredients: Purified Water (Acqua), Capryic/Capic Triglyceride, C12-15 Alkyl Benzoate, Glycerin, Cetyl Alcohol, Stearyl Alcohol, Isopropyl Myristate, Propylene Glycol, Ceteareth-6,Ceteareth-25, Dimethocone, Glyceryl Stearate, Stearic Acid, Tocopherol Acetate(Vitamin E), Alpha Bisabolol, Triethanolamine, Diazolidinyl Urea, Methylparaben, Propylparaben, Allantoin, BHT.

PACKAGE LABEL

Vienna Health and Beauty - by Minh Le, M.D. SUNBLOCK - UVA/UVB Protection - SPF30